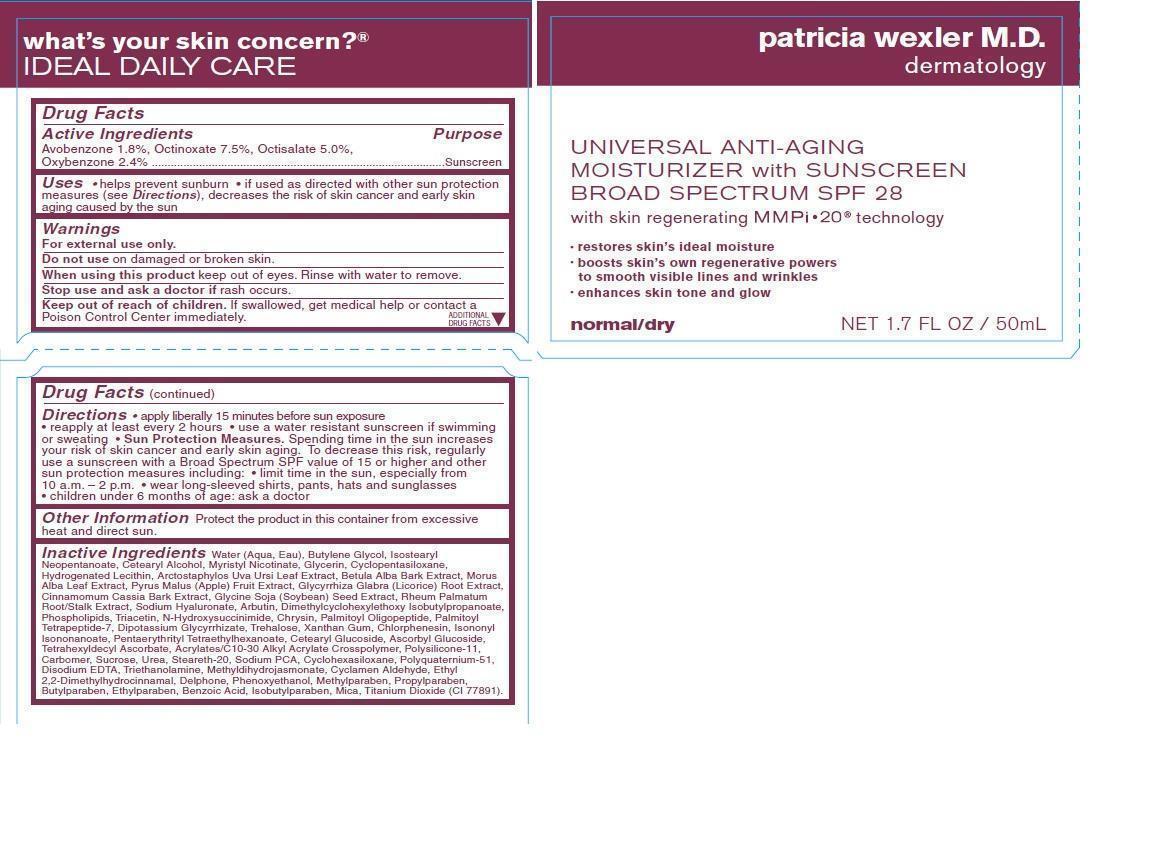 DRUG LABEL: Patricia Wexler Universal Anti-Aging Moisturizer with Sunscreen Broad Spectrum SPF 28
NDC: 62670-8043 | Form: LOTION
Manufacturer: Bath & Body Works, Inc.
Category: otc | Type: HUMAN OTC DRUG LABEL
Date: 20130829

ACTIVE INGREDIENTS: AVOBENZONE 1.8 g/100 mL; OCTINOXATE 7.5 g/100 mL; OCTISALATE 5.0 g/100 mL; OXYBENZONE 2.4 g/100 mL
INACTIVE INGREDIENTS: WATER

ACTIVE INGREDIENTS

Avobenzone 1.8%, Octinoxate 7.5%, Octisalate 5.0%, Oxybenzone 2.4%

PURPOSE

Sunscreen

USES

- helps prevent sunburn
- if used as directed with other sun protection measures (see Directions), decreases the risk of skin cancer and early skin aging caused by the sun

WARNINGS

For external use only.

DO NOT USE

on damaged or broken skin.

WHEN USING THIS PRODUCT

keep out of eyes. Rinse with water to remove.

STOP USE AND ASK A DOCTOR IF

rash occurs.

KEEP OUT OF REACH OF CHILDREN.

If swallowed, get medical help or contact a Poison Control Center immediately.

DIRECTIONS

- apply liberally 15 minutes before sun exposure
- reapply at least every 2 hours
- use a water resistant sunscreen if swimming or sweating
- Sun Protection Measures. Spending time in the sun increases your risk of skin cancer and early skin aging. To decrease this risk, regularly use a sunscreen with a Broad Spectrum SPF value of 15 or higher and other sun protection measures including:
- limit time in the sun, especially from 10 a.m. - 2 p.m.
- wear long-sleeved shirts, pants, hats and sunglasses
- children under 6 months of age: ask a doctor

OTHER INFORMATION

Protect the product in this container from excessive heat and direct sun.

INACTIVE INGREDIENTS

Water (Aqua, Eau), Butylene Glycol, Isostearyl Neopentanoate, Cetearyl Alcohol, Myristyl Nicotinate, Glycerin, Cyclopentasiloxane, Hydrogenated Lecithin, Arctostaphylos Uva Ursi Leaf Extract, Betula Alba Bark Extract, Morus Alba Leaf Extract, Pyrus Malus (Apple) Fruit Extract, Glycyrrhiza Glabra (Licorice) Root Extract, Cinnamomum Cassia Bark Extract, Glycine Soja (Soybean) Seed Extract, Rheum Palmatum Root/Stalk Extract, Sodium Hyaluronate, Arbutin, Dimethylcyclohexylethoxy Isobutylpropanoate, Phospholipids, Triacetin, N-Hydroxysuccinimide, Chrysin, Palmitoyl Oligopeptide, Palmitoyl Tetrapeptide-7, Dipotassium Glycyrrhizate, Trehalose, Xanthan Gum, Chlorphenesin, Isononyl Isononanoate, Pentaerythrityl Tetraethylhexanoate, Cetearyl Glucoside, Ascorbyl Glucoside, Tetrahexyldecyl Ascorbate, Acrylates/C10-30 Alkyl Acrylate Crosspolymer, Polysilicone-11, Carbomer, Sucrose, Urea, Steareth-20, Sodium PCA, Cyclohexasiloxane, Polyquaternium-51, Disodium EDTA, Triethanolamine, Methyldihydrojasmonate, Cyclamen Aldehyde, Ethyl 2,2-Dimethylhydrocinnamal, Delphone, Phenoxyethanol, Methylparaben, Propylparaben, Butylparaben, Ethylparaben, Benzoic Acid, Isobutylparaben, Mica, Titanium Dioxide (CI 77891).

COMPANY INFORMATION

Bath & Body Works, Distr.

Reynoldsburg, Ohio 43068

1-800-395-1001

www.bathandbodyworks.com